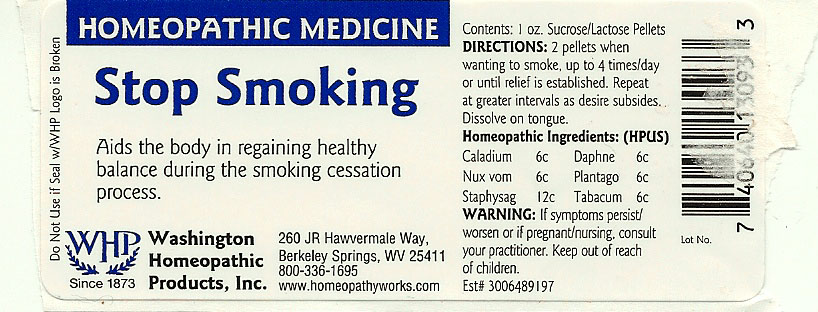 DRUG LABEL: Stop Smoking
NDC: 68428-025 | Form: PELLET
Manufacturer: Washington Homeopathic Products
Category: homeopathic | Type: HUMAN OTC DRUG LABEL
Date: 20191223

ACTIVE INGREDIENTS: DIEFFENBACHIA SEGUINE 6 [hp_C]/28 g; DAPHNE ODORA BARK 6 [hp_C]/28 g; STRYCHNOS NUX-VOMICA SEED 6 [hp_C]/28 g; PLANTAGO MAJOR 6 [hp_C]/28 g; DELPHINIUM STAPHISAGRIA SEED 6 [hp_C]/28 g; TOBACCO LEAF 6 [hp_C]/28 g
INACTIVE INGREDIENTS: SUCROSE; LACTOSE

DRUG FACTS

ACTIVE INGREDIENTS

CALADIUM 6C

DAPHNE 6C

NUX VOM 6C

PLANTAGO 6C

STAPHYSAG 12C

TABACUM 6C

USES

Aids the body in regaining healthy balance during the smoking cessation process.

KEEP OUT OF REACH OF CHILDREN

Keep this and all medicines out of reach of children.

INDICATIONS

CALADIUM Motion sickness

DAPHNE Bad breath

NUX VOM Vomiting

PLANTAGO Earache

STAPHYSAG Anger

TABACUM Sea sickness

STOP USE AND ASK DOCTOR

If symptoms persist/worsen or if pregnant/nursing, stop use and consult your practitioner.

DIRECTIONS

Adults 2 pellets every 3 hours for 2 days. Then 2 pellets morning and night for 2 weeks.

Children: 1 pellet. Repeat as necessary.

INACTIVE INGREDIENTS

Sucrose/Lactose

PRINCIPAL DISPLAY PANEL

Enter section text here